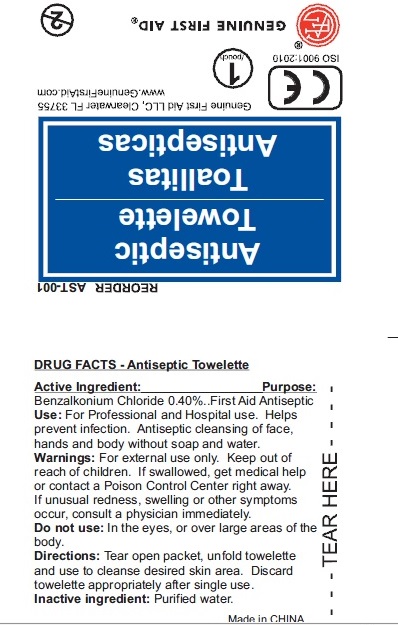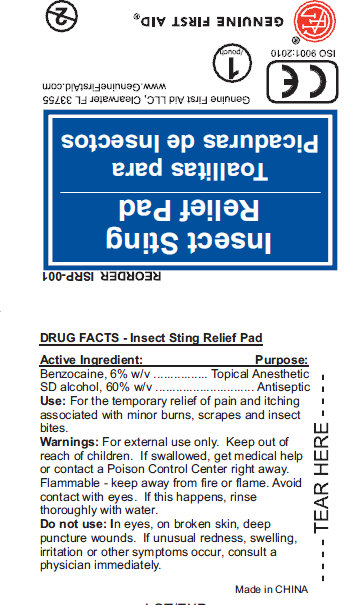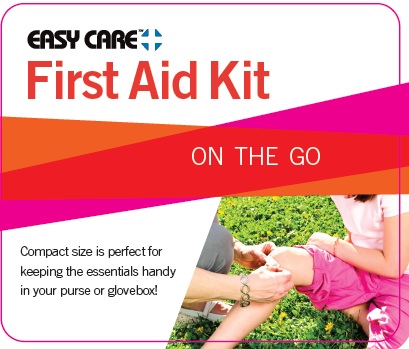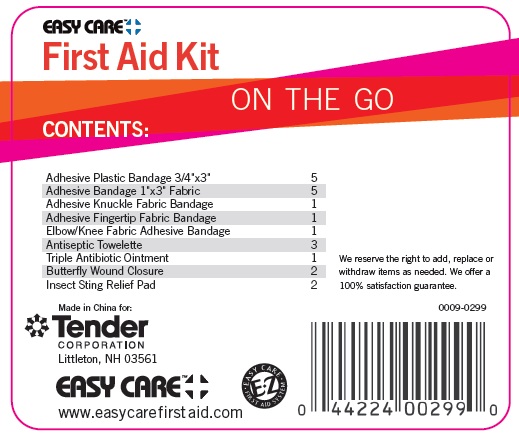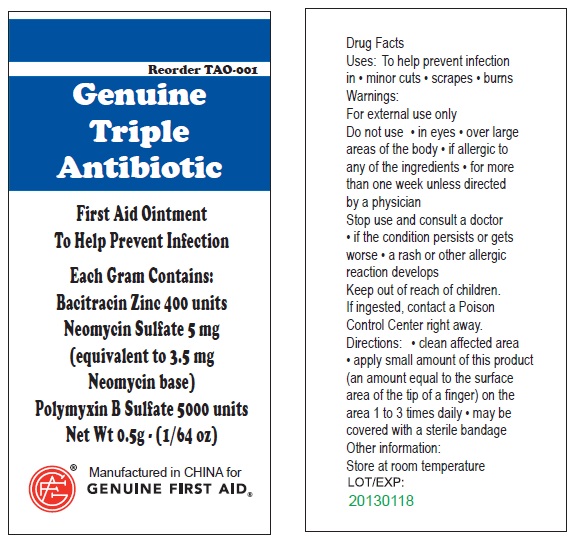 DRUG LABEL: Easy Care First Aid
NDC: 44224-0299 | Form: KIT | Route: TOPICAL
Manufacturer: Tender Corp dba Adventure Medical Kits
Category: otc | Type: HUMAN OTC DRUG LABEL
Date: 20110407

ACTIVE INGREDIENTS: BENZALKONIUM CHLORIDE 0.4 mL/100 mL; BENZOCAINE 6 mL/100 mL; ALCOHOL 60 mL/100 mL; BACITRACIN ZINC 400 [iU]/1 g; NEOMYCIN SULFATE 5 mg/1 g; POLYMYXIN B SULFATE 5000 [iU]/1 g
INACTIVE INGREDIENTS: WATER; WATER; WATER

ANTISEPTIC TOWELETTE

DRUG FACTS:

Active Ingredient purpose

Benzalkonium Chloride 0.40% First Aid Antiseptic

Purpose

First Aid Antiseptic

INDICATIONS AND USAGE

For professional and hospital use. helps prevent infection. antiseptic cleansing of face hand and body without soap and water.

Warnings: For external use only.

Keep out of reach of children. If swallowed, get medical help or contact a Poison Control Center right away. If unusual redness, swelling or other symptoms occur, consult a physician immediately.

Do Not Use: In the eyes, or over large areas of the body

Directions;

Tear open packet, unfold towelette and use to cleanse desired skin area. Discard towelette appropriately after single use.

Inactive Ingredient: Purified Water

PACKAGE LABEL

REORDER AST-001

ANTISEPTIC TOWELETTES

TOALLITAS ANTISEPTICAS

Genuine First Aid, LLC, Clearwater, FL 33755

www.genuinefirstaid.com

GENUNIE FIRST AID

MADE IN CHINA

ACTIVE INGREDIENT

DRUG FACTS- Insect Sting Relief Pad

Active Ingredient: Purpose

Benzocaine, 6% w/v topical anesthetic

SD Alcohol, 60% w/v Antiseptic

INDICATIONS AND USAGE

Use: For the temporary relief of pain and itching associated with minor burns, scrapes and insect bites.

WARNINGS

Warnings: For external use only. Keep out of reach of children. If Swallowed get medical help or contact a Poison Control Center right away. Flammable - keep away from fire or flame. Avoid contact with eyes. If this happens, rinse thoroughly with water.

do not use: in eyes on broken skin, deep puncture wounds. If unusual redness, swelling, irritation or other symptoms occur, consult a physician immediately

PACKAGE LABEL

REORDER ISRP -001

INSECT STING RELIEF PAD

TOALLITAS PARA PICADURAS DE INSECTOS

Genuine First Aid, LLC, Clearwater, FL 33755

www.geniunefirstaid.com

GENUINE FIRST AID

MADE IN CHINA

PACKAGE LABEL

ADVENTURE MEDICAL KITS
1PERSON
FIRST AID [.5]
MEDICAL SUPPLIES AND SURVIVAL TOOLS

PACKAGE LABEL

SURVIVAL TOOLS

1 Slim Rescue Howler Whistle

6 antiseptic wound wipe

1 sting relief wipe

10 Bandage, adhesive, fabric 1" x 3"

2 Bandage, Adhesive, Fabric, Knuckle

1 Bandage Adhesive, Extra Large

2 Bandage, Butterfly Closure

4 Dressing, Gauze, Sterile 2"x2"

25% off your first refill order at

registeryourkit.com

Active Ingredients

Active Ingredient: .........Bacitracin Zinc 400 units

Neomycin Sulfate 5mg (equivalent to 3.5 mg Neomycin base)

Polymyxin B Sulfate 5000 units

Purpose

Triple Antibiotic

INDICATIONS AND USAGE

Uses: To help prevent infection in:
minor cuts; scrapes; burns

Warnings

For external use only.

Do not use: in eyes; over large areas of the body;

If allergic to any of the ingredients; for more than one week unless directed by a physician.

Stop use and consult a doctor:

if the condition persists or gets worse; a rash or other allergic reaction develops

Keep out of reach of children.

If ingested, contact a Poison

Control Center right away.

Directions

Directions: clean affected area; apply small amount of this product (an amount equal to the surface area of the tip of a finger) on the area 1 to 3 times daily; may be covered with a sterile bandage

Other information:

Store at room temperature.

Inactive Ingredient

water

PACKAGE LABEL

Genuine Triple Antibiotic

First Aid Ointment

To Help Prevent Infection

Each Gram Contains:

Bacitracin Zinc 400 units

Neomycin Sulfate 5 mg

(equivalent to 3.5 mg

Neomycin base)

Polymyxin B Sulfate 5000 units

Net Wt. 0.5g ; (1/64 oz)

Manufactured in CHINA for

GENUINE FIRST AID.

Triple Antibiotic Ointment 10pcs

Net wt. 0.9g (1/32oz)

100
Triple Antibiotic